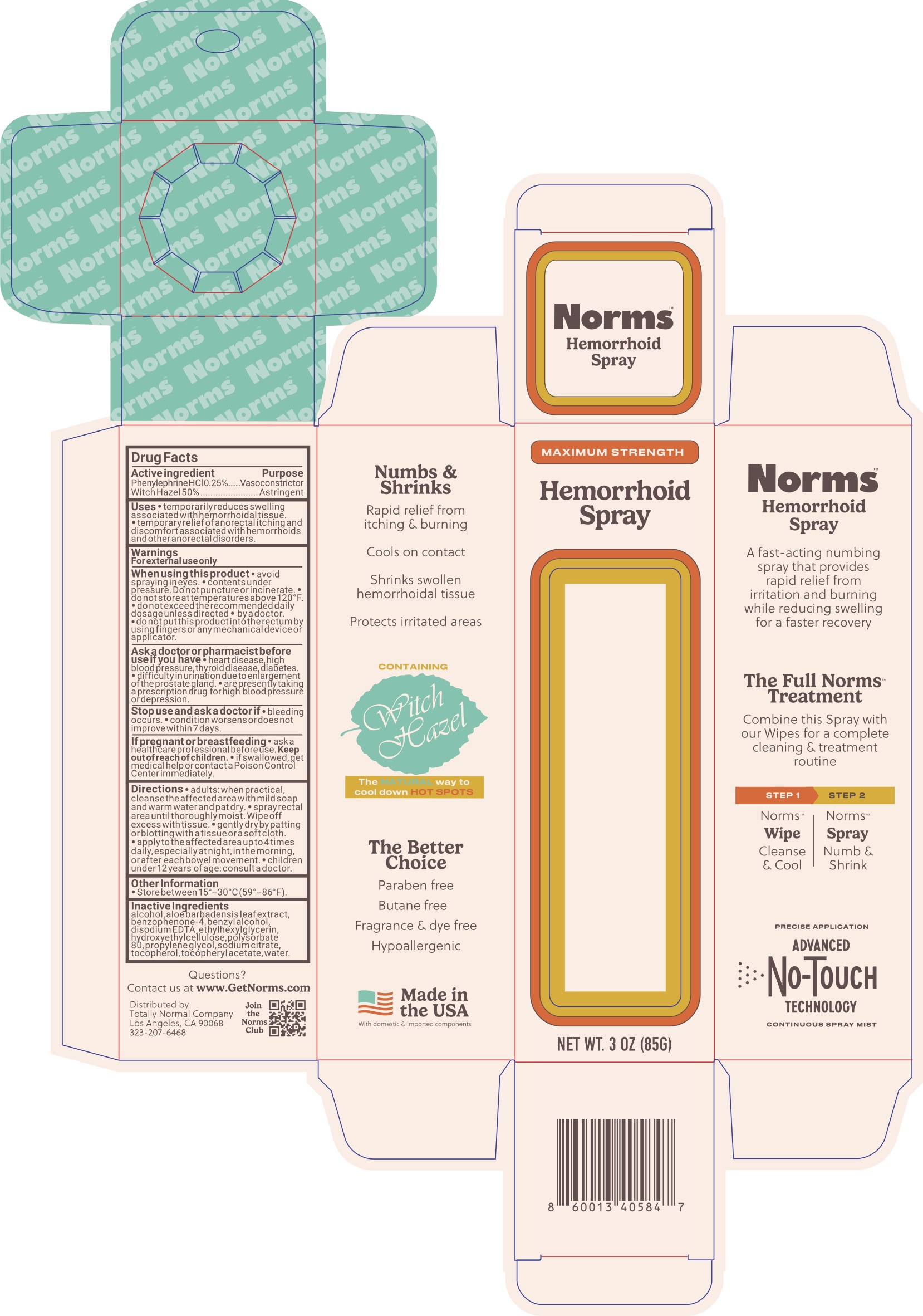 DRUG LABEL: Norms Hemorrhoid
NDC: 85996-135 | Form: SPRAY
Manufacturer: Totally Normal Company
Category: otc | Type: HUMAN OTC DRUG LABEL
Date: 20250817

ACTIVE INGREDIENTS: WITCH HAZEL 50 g/100 g; PHENYLEPHRINE HYDROCHLORIDE 0.25 g/100 g
INACTIVE INGREDIENTS: SULISOBENZONE; ETHYLHEXYLGLYCERIN; PROPYLENE GLYCOL; ALOE; ALCOHOL; BENZYL ALCOHOL; EDETATE DISODIUM; HYDROXYETHYL CELLULOSE, UNSPECIFIED; SODIUM CITRATE; .ALPHA.-TOCOPHEROL ACETATE; POLYSORBATE 80; WATER; TOCOPHEROL

Norms Hemorrhoid Spray

ACTIVE INGREDIENT

Phenylephrine HCl 0.25%, Witch Hazel 50%

PURPOSE

Vasoconstrictor, Astringent

INDICATIONS AND USAGE

Temporarily reduces swelling associated with hemorrhoidal tissue. Temporary relief of anorectal itching and discomfort associated with hemorrhoids and other anorectal disorders.

WARNINGS

For external use only.

When using this product avoid spraying in eyes, contents under pressure. Do not puncture or incinerate. Do not store at temperatures above 120F, do not exceed recommended daily dosage unless directed by a doctor, do not put this product in the rectum by using fingers or any mechanical device or applicator.

Ask a doctor before use if you have heart disease, high blood pressure, thyroid disease, diabetes, difficulty in urination due to enlargement of the prostate gland, presently taking a prescription for high blood pressure or depression.

Stop use and ask a doctor if bleeding occurs, condition worsens or does not improve within 7 days.

PREGNANCY OR BREAST FEEDING

Ask a healthcare or professional before use.

KEEP OUT OF REACH OF CHILDREN

If swallowed, seek medical help or contact a Poison Control Center immediately.

DOSAGE AND ADMINISTRATION

Adults: when practical, cleanse the affected area with mild soap and warm water and pat dry. Spray the rectal area until thoroughly moist. Wipe off excess with a tissue, gently dry by patting or blotting with a tissue or a soft cloth, apply to the affected area up to 4 times daily especially at night in the morning or after each bowel movement. For children under 12 years of age, consult a doctor.

INACTIVE INGREDIENT

Alcohol, Aloe Barbadensis Leaf Extract, Benzophenone-4, Benzyl Alcohol, Disodium EDTA, Ethylhexylglycerin, Hydroxyethylcellulose, Polysorbate 80, Propylene Glycol, Sodium Citrate, Tocopherol, Tocopheryl Acetate, Water.